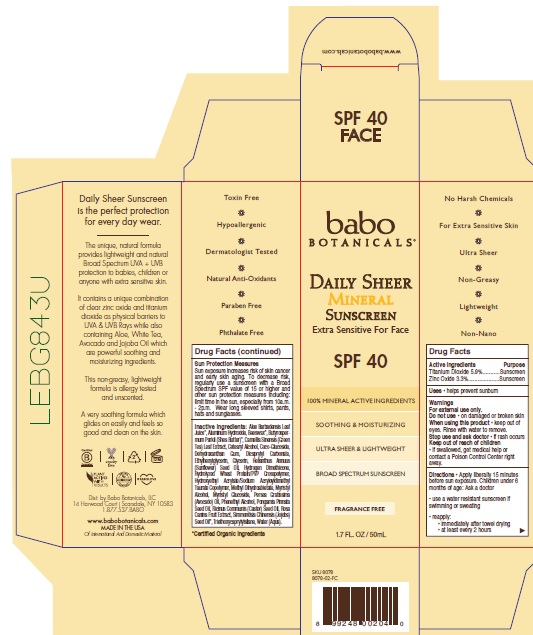 DRUG LABEL: Babo Botanicals Daily Sheer Mineral Sunscreen SPF 40
NDC: 79265-8708 | Form: LOTION
Manufacturer: Babo Botanicals, Inc.
Category: otc | Type: HUMAN OTC DRUG LABEL
Date: 20241212

ACTIVE INGREDIENTS: ZINC OXIDE 33 mg/1 mL; TITANIUM DIOXIDE 59 mg/1 mL
INACTIVE INGREDIENTS: TRIETHOXYCAPRYLYLSILANE; ALUMINUM HYDROXIDE; ETHYLHEXYLGLYCERIN; JOJOBA OIL; CASTOR OIL; ROSA CANINA FRUIT; PHENYLETHYL ALCOHOL; CETOSTEARYL ALCOHOL; DEHYDROXANTHAN GUM; SUNFLOWER OIL; METHYL DIHYDROABIETATE; HYDROGEN DIMETHICONE (13 CST); HYDROXYETHYL ACRYLATE/SODIUM ACRYLOYLDIMETHYL TAURATE COPOLYMER (45000 MPA.S AT 1%); DICAPRYLYL CARBONATE; AVOCADO OIL; WATER; SHEA BUTTER; MYRISTYL ALCOHOL; MYRISTYL GLUCOSIDE; KARUM SEED OIL; COCO GLUCOSIDE; ALOE VERA LEAF; GLYCERIN; YELLOW WAX; GREEN TEA LEAF

Babo Botanicals Daily Sheer Mineral Sunscreen SPF 40

Active Ingredients

Titanium Dioxide 5.9%

Zinc Oxide 3.3%

Purpose

Sunscreen

Uses

• Helps prevent sunburn.

Warnings

For external use only.

Do not use

on damaged or broken skin.

When using this product

- keep out of eyes. Rinse with water to remove.

Stop use and ask doctor

- if rash occurs.

Keep out of reach of children.

If swallowed, get medical help or contact a Poison Control Center right away.

Directions

- Apply liberally 15 minutes before sun exposure. Children under 6 months of age: Ask a doctor
- use a water resistant sunscreen if swimming or sweating
- reapply:
- immediately after towel drying
- at least every 2 hours

Sun Protection Measures Sun exposure increases risk of skin cancer and early skin aging. To decrease risk, regularly use a sunscreen with a Broad Spectrum SPF value of 15 or higher and other sun protection measures including: limit time in the sun, especially from 10a.m. - 2p.m. Wear long sleeved shirts, pants, hats and sunglasses.

Inactive ingredients

Aloe Barbadensis Leaf Juice*, Aluminum Hydroxide, Beeswax*, Butyrospermum Parkii (Shea Butter)*, Camellia Sinensis (Green Tea) Leaf Extract, Cetearyl Alcohol, Coco-Glucoside, Dehydroxanthan Gum, Dicaprylyl Carbonate, Ethylhexylglycerin, Glycerin, Helianthus Annuus (Sunflower) Seed Oil, Hydrogen Dimethicone, Hydrolyzed Wheat Protein/PVP Crosspolymer, Hydroxyethyl Acrylate/Sodium Acryloyldimethyl Taurate Copolymer, Methyl Dihydroabietate, Myristyl Alcohol, Myristyl Glucoside, Persea Gratissima (Avocado) Oil, Phenethyl Alcohol, Pongamia Pinnata Seed Oil, Ricinus Communis (Castor) Seed Oil, Rosa Canina Fruit Extract, Simmondsia Chinensis (Jojoba) Seed Oil*, Triethoxycaprylylsilane, Water (Aqua).

*Certified Organic Ingredients